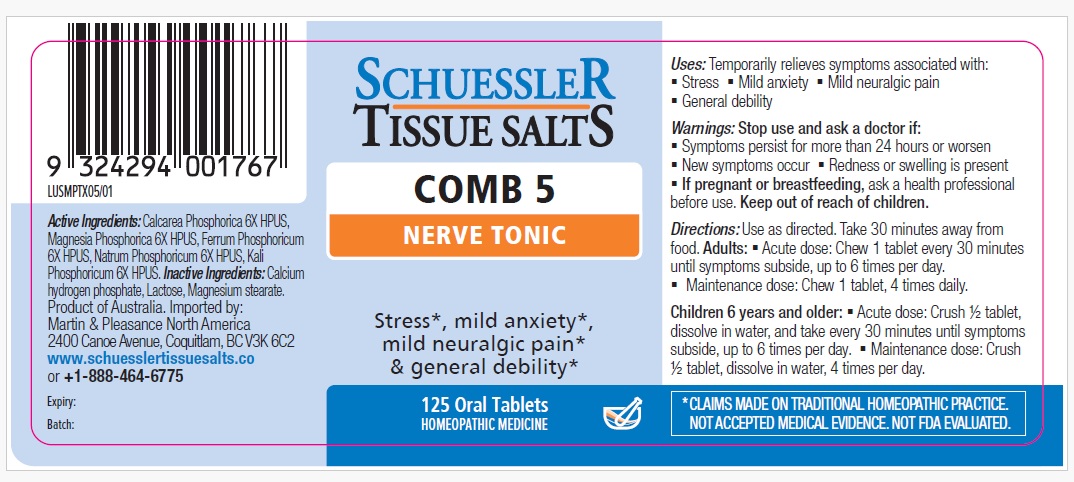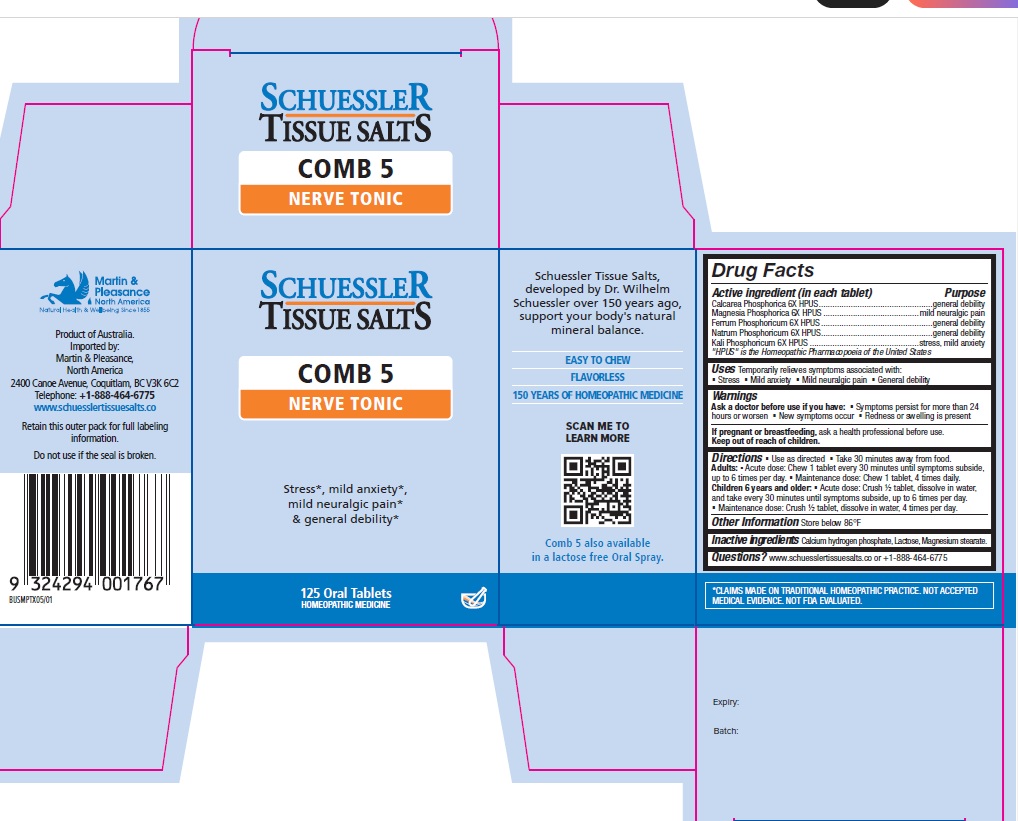 DRUG LABEL: Schuessler Tissue Salts Comb 5 Nerve Tonic
NDC: 84999-025 | Form: TABLET, CHEWABLE
Manufacturer: Martin & Pleasance Pty Ltd
Category: homeopathic | Type: HUMAN OTC DRUG LABEL
Date: 20250813

ACTIVE INGREDIENTS: TRIBASIC CALCIUM PHOSPHATE 6 [hp_X]/1 1; MAGNESIUM PHOSPHATE, DIBASIC 6 [hp_X]/1 1; FERROUS PHOSPHATE 6 [hp_X]/1 1; SODIUM PHOSPHATE, DIBASIC, ANHYDROUS 6 [hp_X]/1 1; DIBASIC POTASSIUM PHOSPHATE 6 [hp_X]/1 1
INACTIVE INGREDIENTS: LACTOSE MONOHYDRATE; MAGNESIUM STEARATE; ANHYDROUS DIBASIC CALCIUM PHOSPHATE

Active Ingredients Purpose

Calcarea Phosphorica 6X HPUS..................................................general debility
Magnesia Phosphorica 6X HPUS ..........................................mild neuralgic pain
Ferrum Phosphoricum 6X HPUS .................................................general debility
Natrum Phosphoricum 6X HPUS.................................................general debility
Kali Phosphoricum 6X HPUS ................................................stress, mild anxiety

" HPUS" is the Homeopathic Pharmacopoeia of the United States

Uses

Temporarily relieves symptoms associated with

- Stress
- Mild anxiety
- Mild neuralgic pain
- General debility

Warnings

Ask a doctor before use if you have:

- Symptoms persist for more than 24 hours or worsen
- New symptoms occur
- Redness or swelling is present

If pregnant or breastfeeding, ask a health professional before use.
Keep out of reach of children.

Directions

- Use as directed
- Take 30 minutes away from food.

Adults:

- Acute dose: Chew 1 tablet every 30 minutes until symptoms subside, up to 6 times per day.
- Maintenance dose: Chew 1 tablet, 4 times daily.

Children 6 years and older:

- Acute dose: Crush ½ tablet, dissolve in water, and take every 30 minutes until symptoms subside, up to 6 times per day.
- Maintenance dose: Crush ½ tablet, dissolve in water, 4 times per day.

Other Information

Store below 86°F

Inactive Ingredients

Calcium hydrogen phosphate, Lactose, Magnesium stearate.

Questions? www.schuesslertissuesalts.co or + 1-888-464-6775